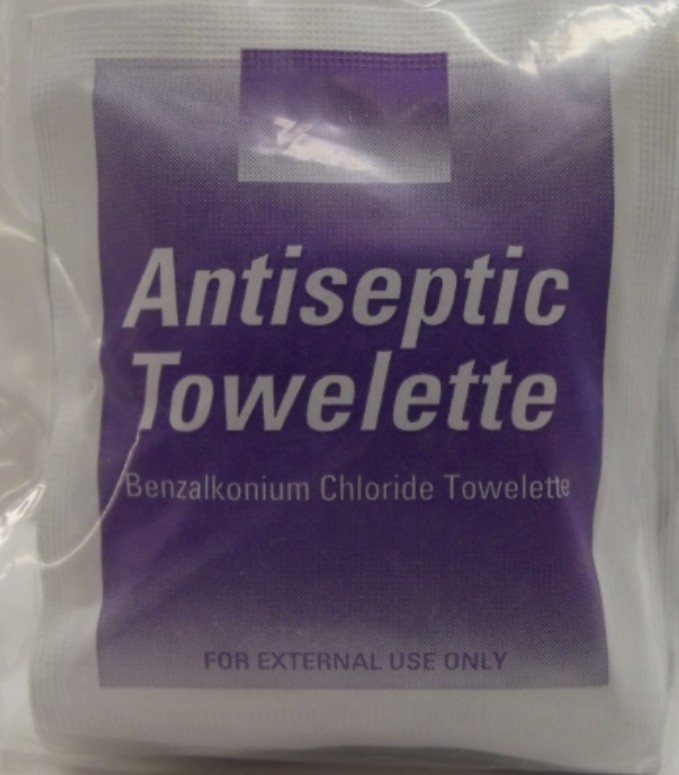 DRUG LABEL: First Aid Direct Antiseptic Wipe
NDC: 42961-127 | Form: SPONGE
Manufacturer: Cintas Corporation
Category: otc | Type: HUMAN OTC DRUG LABEL
Date: 20250929

ACTIVE INGREDIENTS: BENZALKONIUM CHLORIDE .133 mg/100 mL
INACTIVE INGREDIENTS: SODIUM BICARBONATE; WATER

First Aid Direct Antiseptic Wipe

Active ingredient (in each towelette)

Benzalkonium Chloride 0.133%

Purpose

first aid antiseptic

Uses

first aid to reduce bacteria in minor cuts, scrapes and burns

Warnings

For external use only

Do not use

- in the eyes or apply over large areas of the body
- longer than 1 week unless directed by a doctor

Ask a doctor before use if you have

- deep or puncture wounds
- animal bites
- serious burns

Stop use and ask a doctor if

- condition persists or gets worse

Keep out of reach of children. If swallowed, get medical help or contact a Poison Control Center right away.

Directions

- tear open packet, unfold, use and discard
- clean the affected area
- maybe covered with a sterile bandage. If bandaged, let dry first.

Other information

- do not use if packet is torn, cut or opened
- store at room temperature

Inactive ingredients

purified water, sodium bicarbonate

Questions? 1-877-973-2811

Principal Display Panel

Antiseptic Wipe

One Wipe Saturated with Benzalkonium Chloride

EXTERNAL USE ONLY